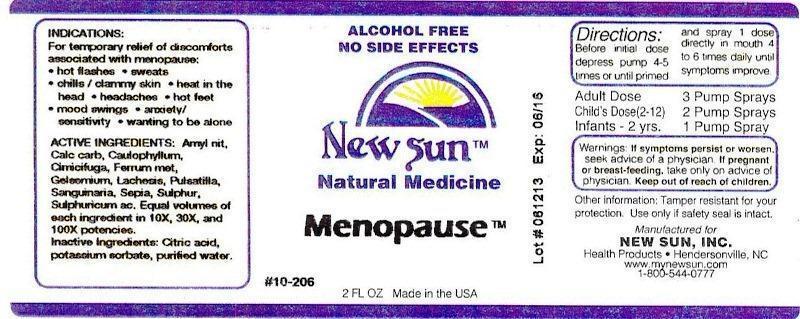 DRUG LABEL: Menopause
NDC: 66579-0080 | Form: LIQUID
Manufacturer: New Sun Inc.
Category: homeopathic | Type: HUMAN OTC DRUG LABEL
Date: 20141024

ACTIVE INGREDIENTS: AMYL NITRITE 10 [hp_X]/59 mL; OYSTER SHELL CALCIUM CARBONATE, CRUDE 10 [hp_X]/59 mL; CAULOPHYLLUM THALICTROIDES ROOT 10 [hp_X]/59 mL; BLACK COHOSH 10 [hp_X]/59 mL; IRON 10 [hp_X]/59 mL; GELSEMIUM SEMPERVIRENS ROOT 10 [hp_X]/59 mL; LACHESIS MUTA VENOM 10 [hp_X]/59 mL; PULSATILLA VULGARIS 10 [hp_X]/59 mL; SANGUINARIA CANADENSIS ROOT 10 [hp_X]/59 mL; SEPIA OFFICINALIS JUICE 10 [hp_X]/59 mL; SULFUR 10 [hp_X]/59 mL; SULFURIC ACID 10 [hp_X]/59 mL
INACTIVE INGREDIENTS: CITRIC ACID MONOHYDRATE; POTASSIUM SORBATE; WATER

Menopause

DOSAGE AND ADMINISTRATION

Directions: Before initial dose depress pump 4-5 times or until primed and spray 1 dose directly in mouth 4 to 6 times daily until symptoms improve.

Adult Dose: 3 Pump Sprays

Child's Dose (2-12): 2 Pump Sprays

Infants - 2 yrs. 1 Pump Spray

WARNINGS

Warnings: If symptoms persist or worsen, seek advice of a physician. If pregnant or breast-feeding, take only on advice of physician.

Keep out of reach of children.

Other information: Tamper resistant for your protection. Use only if safety seal is intact.

PURPOSE

Indications: For temporary relief of discomforts associated with menopause: •hot flashes •sweats •chills/clammy skin •heat in the head •headaches •hot feet •mood swings •anxiety/sensitivity •wanting to be alone

ACTIVE INGREDIENT

Active Ingredients: Amyl nitrosum, Calcarea carbonica, Caulophyllum thalictroides, Cimicifuga racemosa, Ferrum metallicum, Gelsemium sempervirens, Lachesis mutus, pulsatilla, Sanguinaria canadensis, Sepia, Sulphur, Sulphuricum acidum. Equal volumes of each ingredient in 10X, 30X, and 100X potencies.

Inactive Ingredient: Citric acid, potassium sorbate, purified water.

INDICATIONS AND USAGE

Indications: For temporary relief of discomforts associated with menopause:

- hot flashes
- sweats
- chills/clammy skin
- heat in the head
- headaches
- hot feet
- mood swings
- anxiety/sensitivity
- wanting to be alone